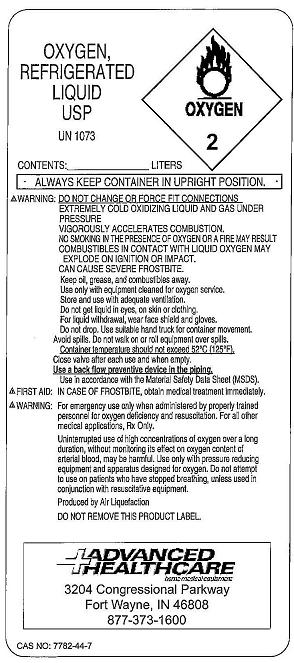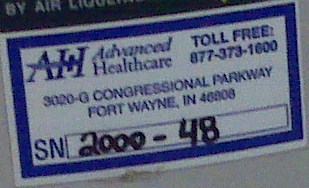 DRUG LABEL: Oxygen
NDC: 65141-0001 | Form: GAS
Manufacturer: CareFirst of Fort Wayne, Inc. dba Advanced Healthcare
Category: prescription | Type: HUMAN PRESCRIPTION DRUG LABEL
Date: 20091026

ACTIVE INGREDIENTS: Oxygen 99 L/100 L

Oxygen